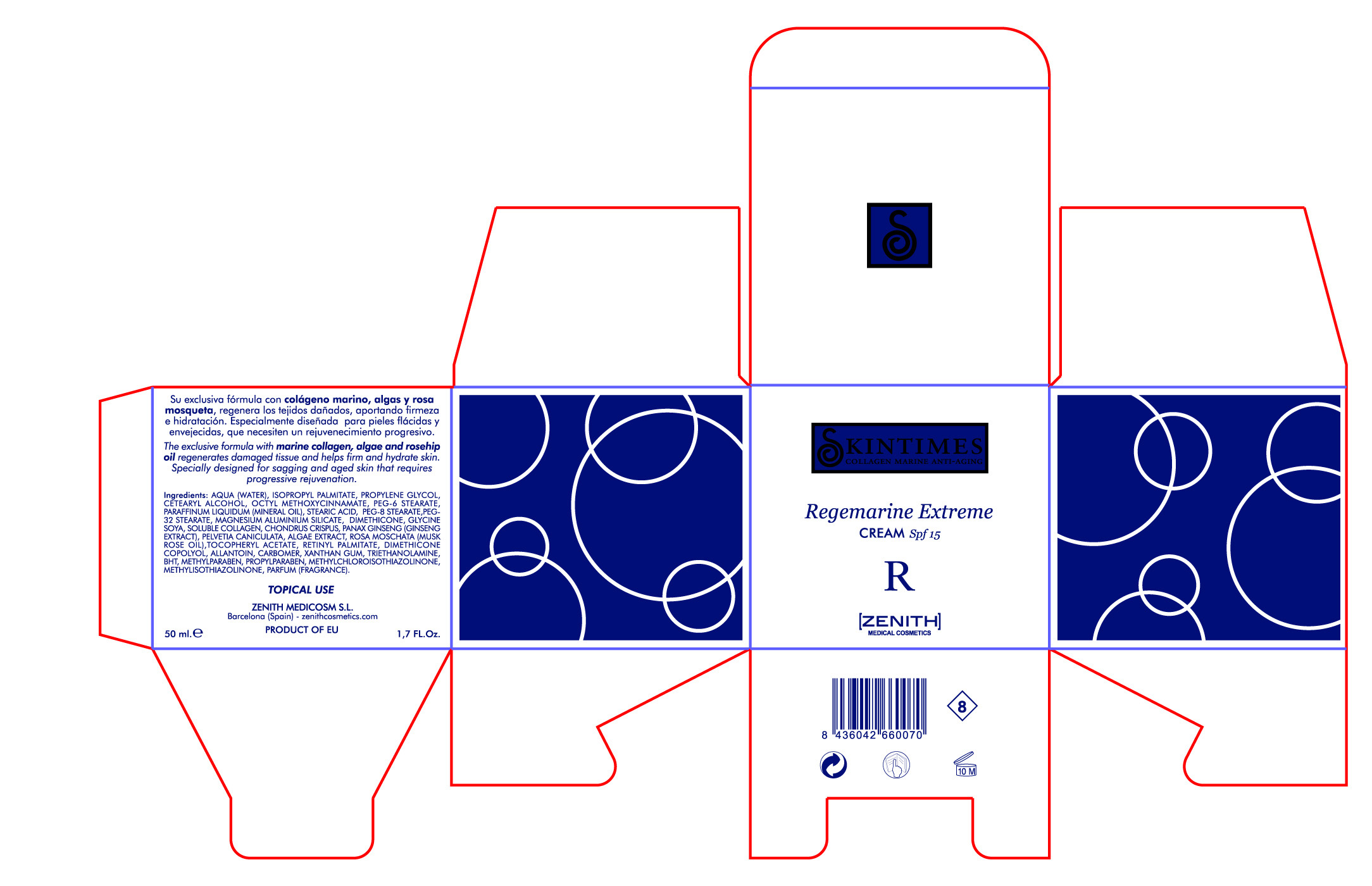 DRUG LABEL: Regemarine
NDC: 42248-107 | Form: CREAM
Manufacturer: Zenith Medicosm SL
Category: otc | Type: HUMAN OTC DRUG LABEL
Date: 20120121

ACTIVE INGREDIENTS: OCTINOXATE 3.75 mL/50 mL
INACTIVE INGREDIENTS: MAGNESIUM ALUMINUM SILICATE; PROPYLPARABEN; ALPHA-TOCOPHEROL ACETATE; DIMETHICONE; XANTHAN GUM; ROSA MOSCHATA OIL; WATER; MINERAL OIL; CETOSTEARYL ALCOHOL; PEG-8 STEARATE; TROLAMINE; SOYBEAN; CHONDRUS CRISPUS; BUTYLATED HYDROXYTOLUENE; METHYLISOTHIAZOLINONE; CARBOMER 934; PROPYLENE GLYCOL; METHYLCHLOROISOTHIAZOLINONE; METHYLPARABEN; COLLAGEN, SOLUBLE, FISH SKIN; ISOPROPYL PALMITATE; PEG-6 STEARATE; PEG-32 STEARATE; STEARIC ACID; PANAX GINSENG FRUIT; PEG/PPG-20/23 DIMETHICONE; FUCUS VESICULOSUS; PELVETIA CANALICULATA; ALLANTOIN; VITAMIN A PALMITATE

Drug Facts

Active Ingredient

Octinoxate 7.5%

Description

The exclusive formula with marine collagen, algae and rosehip oil regenerates damaged tissue and helps firm and hydrate skin. Specially designed for sagging and aged skin that requires progressive rejuvenation.

50ml. 1.7 fl. Oz

Warning

TOPICAL USE